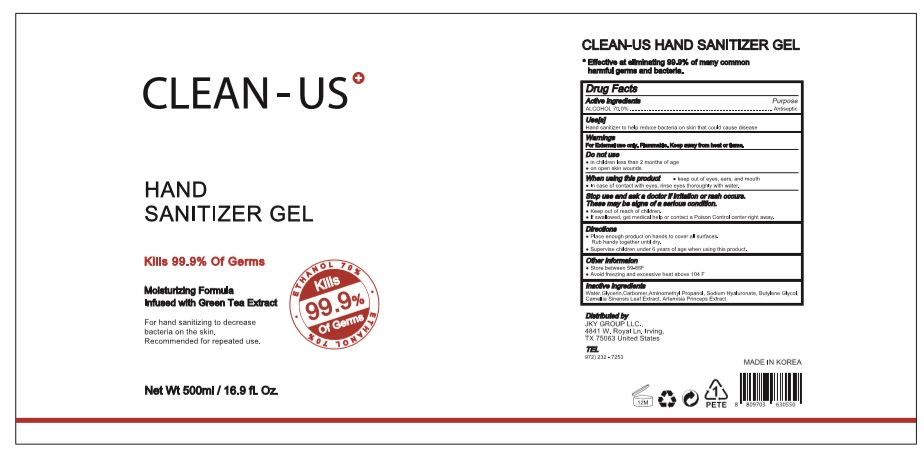 DRUG LABEL: CLEAN-US HAND SANITIZER Gel
NDC: 73823-571 | Form: GEL
Manufacturer: WHAIN COSMETIC
Category: otc | Type: HUMAN OTC DRUG LABEL
Date: 20200429

ACTIVE INGREDIENTS: ALCOHOL 350 mL/500 mL
INACTIVE INGREDIENTS: AMINOMETHYL PROPANEDIOL; GLYCERIN; HYALURONATE SODIUM; BUTYLENE GLYCOL; CARBOMER HOMOPOLYMER, UNSPECIFIED TYPE; WATER; ARTEMISIA PRINCEPS LEAF; GREEN TEA LEAF

[CLEAN-US HAND SANITIZER GEL ] 1 * 500 ml : 73823-571-01